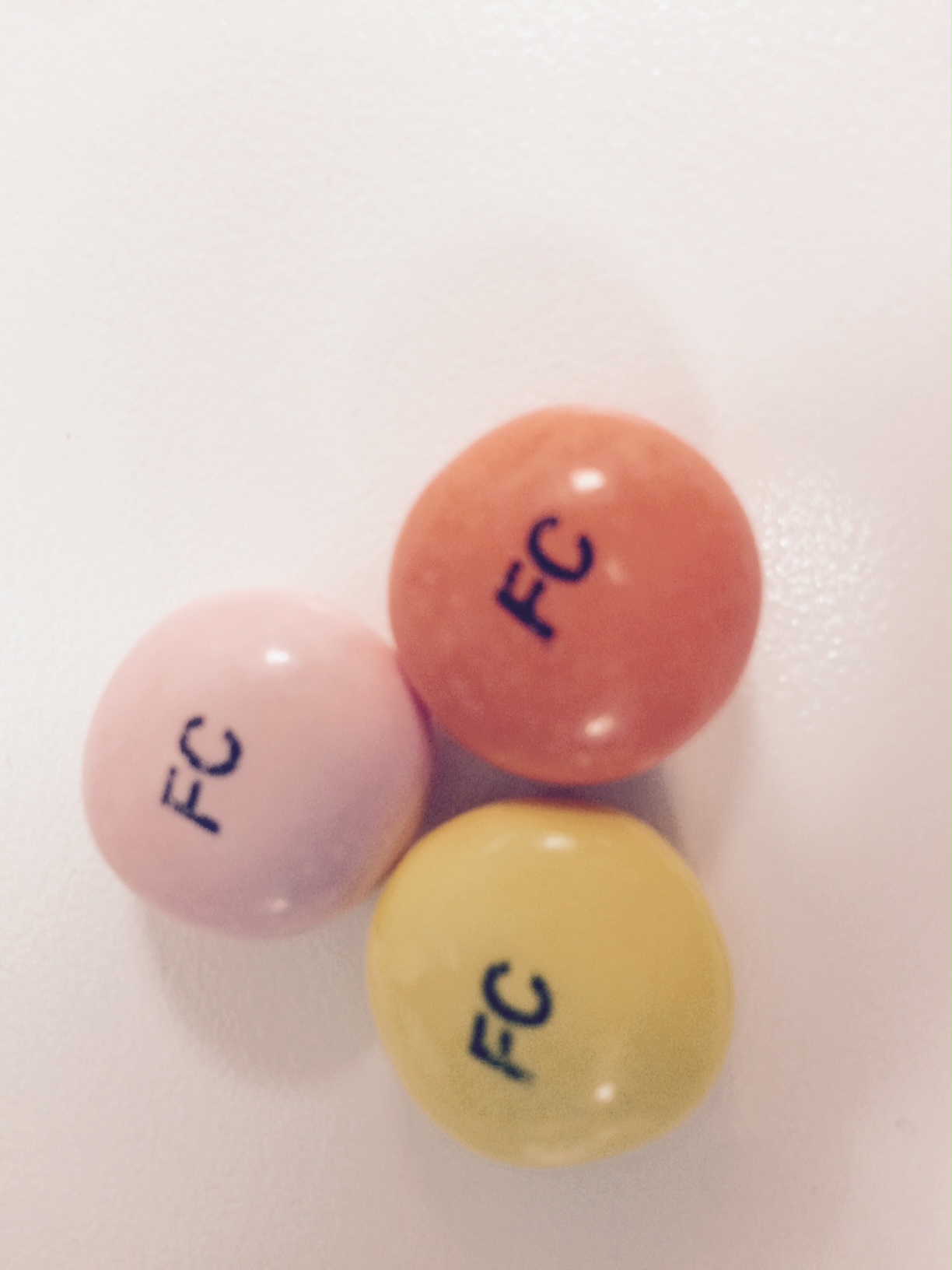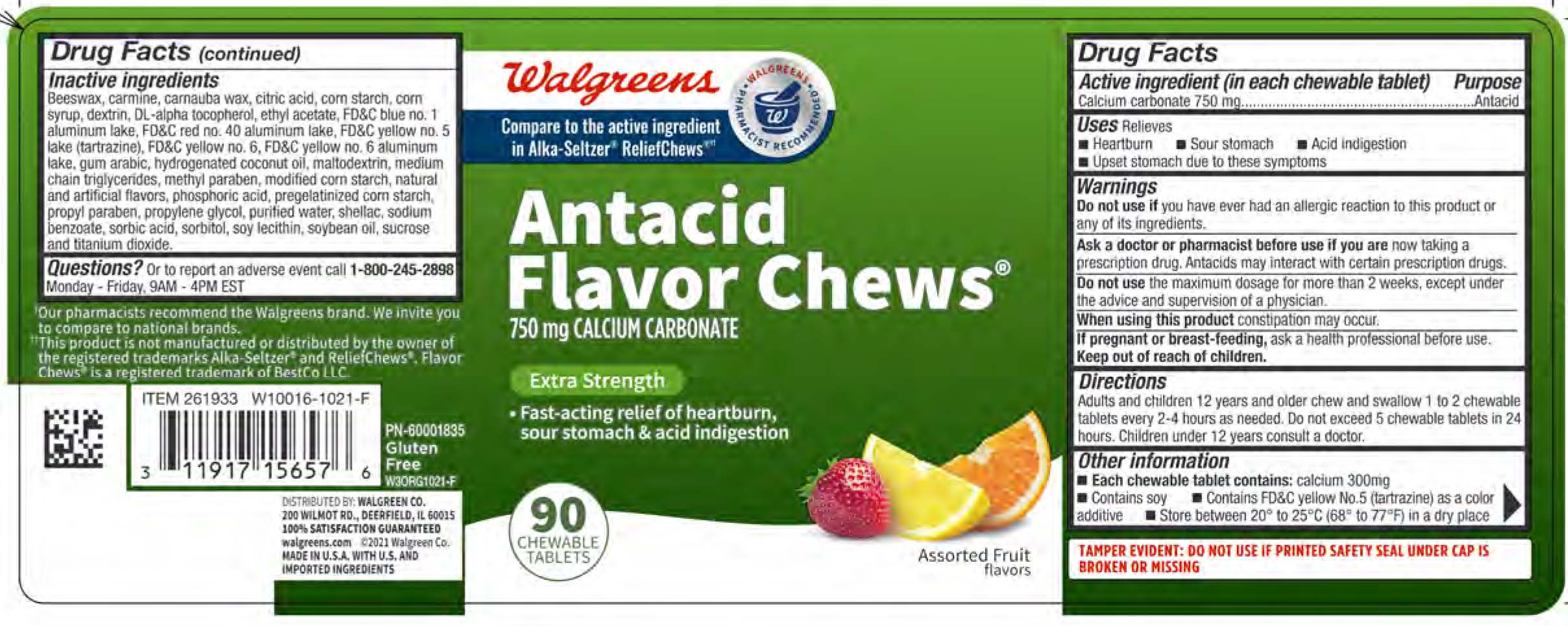 DRUG LABEL: Antacid Flavor Chews
NDC: 0363-1083 | Form: TABLET, CHEWABLE
Manufacturer: Walgreen Co.
Category: otc | Type: HUMAN OTC DRUG LABEL
Date: 20251221

ACTIVE INGREDIENTS: CALCIUM CARBONATE 750 mg/1 1
INACTIVE INGREDIENTS: SUCROSE

Calcium carbonate 750 mg

Active ingredient (in each chewable tablet)

Calcium Carbonate 750 mg

Purpose

Antacid

INDICATIONS AND USAGE

Uses Relieves:

Heartburn

Sour Stomach

Acid indigestion

Upset stomach due to these symptoms

Warnings

Do not use if you have ever had an allergic reaction to this product or any of its ingredients.

Ask a doctor or pharmacist before use if you are now taking a presciption drug. Antacids may interact with certain prescripton drugs.

Do not use the maximum dosage for more than 2 weeks except under the advice and supervision of a physician.

When using this product constipation may occur.

PREGNANCY OR BREAST FEEDING

If pregnant or breast-feeding, ask a health professional before use.

Keep out of reach of children.

Directions

Adults and children 12 years and older chew and swallow 1 to 2 chews every 2-4 hours as needed. Do not exceed 5 chews in 24 hours. children under 12 years consult a doctor.

Other information

- Each chewable tablet contains: calcium 300 mg, magnesium 1 mg
- Contains Soy
- Contains yellow no. 5 (tartrazine) as a color additive
- Store between 20º to 25ºC (68º to 77ºF) in a dry place

INACTIVE INGREDIENT

Inactive ingredients: Beeswax, carmine, carnauba wax, citric acid, corn starch, corn syrup, DL-alpha tocopherol, ethyl acetate, FD&C blue no. 1 aluminum lake, FD&C red no. 40 aluminum lake, FD&C yellow no. 5 lake (tartrazine), FD&C yellow no. 6, FD&C yellow no. 6 aluminum lake, gum arabic, hydrogenated coconut oil, maltodextrin, medium chain triglycerides, methyl paraben, modified corn starch, natural and artificial flavors, phosphoric acid, pregelatinized corn starch, propyl paraben, propylene glycol, purified water, shellac, sodium benzoate, sorbic acid, sorbitol, soy lecithin, soybean oil, sucrose, and titanium dioxide.

QUESTIONS

Questions? Or to report an adverse event call 1-800-245-2898 Monday - Friday, 9AM - 4PM EST